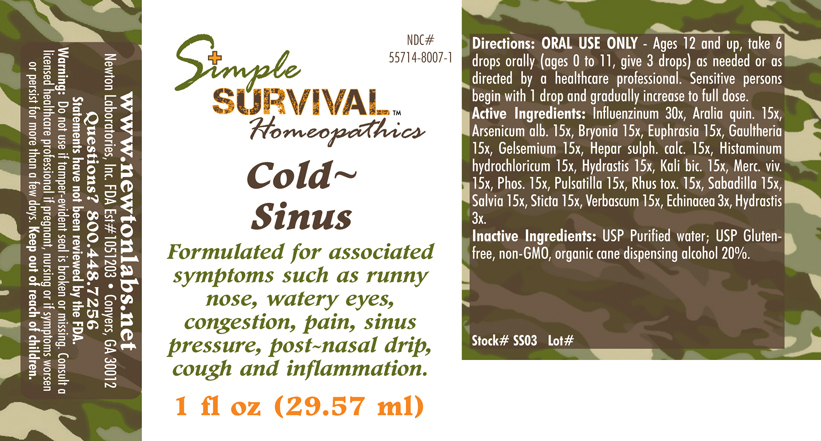 DRUG LABEL: Cold - Sinus 
NDC: 55714-8007 | Form: LIQUID
Manufacturer: Newton Laboratories, Inc.
Category: homeopathic | Type: HUMAN OTC DRUG LABEL
Date: 20140415

ACTIVE INGREDIENTS: Influenza A Virus 30 [hp_X]/1 mL; American Ginseng 15 [hp_X]/1 mL; Arsenic Trioxide 15 [hp_C]/1 mL; Bryonia Alba Root 15 [hp_X]/1 mL; Euphrasia Stricta 15 [hp_X]/1 mL; Gaultheria Procumbens Top 15 [hp_X]/1 mL; Gelsemium Sempervirens Root 15 [hp_X]/1 mL; Calcium Sulfide 15 [hp_X]/1 mL; Histamine Dihydrochloride 15 [hp_X]/1 mL; Goldenseal 15 [hp_X]/1 mL; Potassium Dichromate 15 [hp_X]/1 mL; Mercury 15 [hp_X]/1 mL; Phosphorus 15 [hp_X]/1 mL; Pulsatilla Vulgaris 15 [hp_X]/1 mL; Toxicodendron Pubescens Leaf 15 [hp_X]/1 mL; Schoenocaulon Officinale Seed 15 [hp_X]/1 mL; Sage 15 [hp_X]/1 mL; Lobaria Pulmonaria 15 [hp_X]/1 mL; Verbascum Thapsus 15 [hp_X]/1 mL; Echinacea, Unspecified 3 [hp_X]/1 mL; Influenza B Virus 30 [hp_X]/1 mL
INACTIVE INGREDIENTS: Alcohol

Cold - Sinus

INDICATIONS & USAGE SECTION

Cold - Sinus Formulated for associated symptoms such as runny nose, watery eyes, congestion, pain, sinus pressure, post-nasal drip, cough and inflammation.

DOSAGE & ADMINISTRATION SECTION

Directions: ORAL USE ONLY - Ages 12 and up, take 6 drops orally (ages 0 to 11, give 3 drops) as needed or as directed by a healthcare professional. Sensitive persons begin with 1 drop and gradually increase to full dose.

OTC - ACTIVE INGREDIENT SECTION

Influenzinum 30x, Aralia quin. 15x, Arsenicum alb. 15x, Bryonia 15x, Euphrasia 15x, Gaultheria 15x, Gelsemium 15x, Hepar sulph. calc. 15x, Histaminum hydrochloricum 15x, Hydrastis 15x, Kali bic. 15x, Merc. viv. 15x, Phos. 15x, Pulsatilla 15x, Rhus tox. 15x, Sabadilla 15x, Salvia 15x, Sticta 15x, Verbascum 15x, Echinacea 3x, Hydrastis 3x.

OTC - PURPOSE SECTION

Formulated for associated symptoms such as runny nose, watery eyes, congestion, pain, sinus pressure, post-nasal drip, cough and inflammation.

INACTIVE INGREDIENT SECTION

Inactive Ingredients: USP Purified Water; USP Gluten-free, non-GMO, organic cane dispensing alcohol 20%.

QUESTIONS SECTION

www.newtonlabs.net Newton Laboratories, Inc. FDA Est # 1051203 - Conyers, GA 30012
Questions? 1.800.448.7256

WARNINGS SECTION

Warning: Do not use if tamper - evident seal is broken or missing. Consult a licensed healthcare professional if pregnant, nursing or if symptoms worsen or persist for more than a few days. Keep out of reach of children.

OTC - PREGNANCY OR BREAST FEEDING SECTION

Consult a licensed healthcare professional if pregnant, nursing or if symptoms worsen or persist for more than a few days

OTC - KEEP OUT OF REACH OF CHILDREN SECTION

Keep out of reach of children